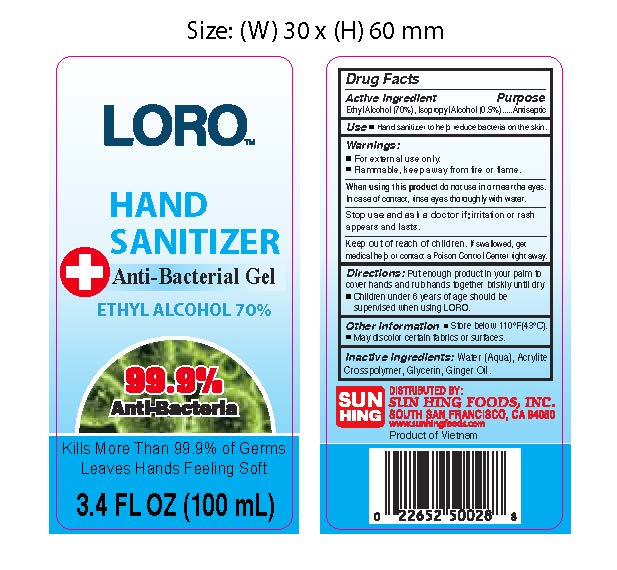 DRUG LABEL: LORO Hand Sanitizer
NDC: 78185-016 | Form: GEL
Manufacturer: Sun Hing Foods Inc
Category: otc | Type: HUMAN OTC DRUG LABEL
Date: 20200330

ACTIVE INGREDIENTS: ALCOHOL 70 mL/100 mL; ISOPROPYL ALCOHOL 0.2 mL/100 mL
INACTIVE INGREDIENTS: GINGER OIL 0.05 mL/100 mL; GLYCERIN 0.25 mL/100 mL; WATER 29 mL/100 mL; CARBOMER INTERPOLYMER TYPE A (55000 CPS) 0.5 mL/100 mL

LORO
HAND SANITIZER
Anti-Bacterial Gel
ETHYL ALCOHOL 70%
3.4 FL OZ (100mL)

This is a hand sanitizer manufactured according to the Temporary Policy for Preparation of Certain Alcohol-Based Hand Sanitizer Products During the Public Health Emergency (CoViD-19); Guidance for Industry.

The hand sanitizer is manufactured using only the following United States Pharmacopoeia (USP) grade ingredients in the preparation of the product (percentage in final product formulation) consistent with World Health Organization (WHO) recommendations:

1. Alcohol (ethanol) (USP or Food Chemical Codex (FCC) grade) (70%, volume/volume (v/v)) in an aqueous solution denatured according to Alcohol and Tobacco Tax and Trade Bureau regulations in 27 CFR part 20.
2. Isopropyl Alcohol (0.2% v/v).
3. Ginger Oil (0.05% v/v)
4. Glycerin (0.25% v/v).
5. Acrylite Crosspolymer (0.5% v/v).
6. Water (29% v/v).

The firm does not add other active or inactive ingredients. Different or additional ingredients may impact the quality and potency of the product.

Active Ingredient(s)

Ethyl Alcohol 70% v/v, Isopropyl Alcohol 0.5% v/v. Purpose: Antiseptic

Purpose

Antiseptic, Hand Sanitizer

Use

Hand Sanitizer to help reduce bacteria on the skin.

Warnings

For external use only. Flammable. Keep away from heat or flame

Do not use

- Children 6 years of age should be supervised when using LORO.

When using this product do not use in or near the eyes. In case of contact, rinse eyes thoroughly with water.
Stop use and ask a doctor if irritation or rash appears and lasts.
Keep out of reach of children. If swallowed, get medical help or contact a Poison Control Center right away.

Stop use and ask a doctor if irritation or rash appears and lasts.

Keep out of reach of children. If swallowed, get medical help or contact a Poison Control Center right away.

Directions

- Place enough product in your palm to cover hands and rub hands together briskly until dry.
- Children 6 years of age should be supervised when using LORO.

Other information

- Store below 110 Degree F (43 Degree C)
- May discolor certain fabrics or surfaces

Inactive ingredients

Water (Aqua), Acrylite Crosspolymer, Glycerin, Ginger Oil.

Package Label - Principal Display Panel

100 mL NDC: 78185-016-01